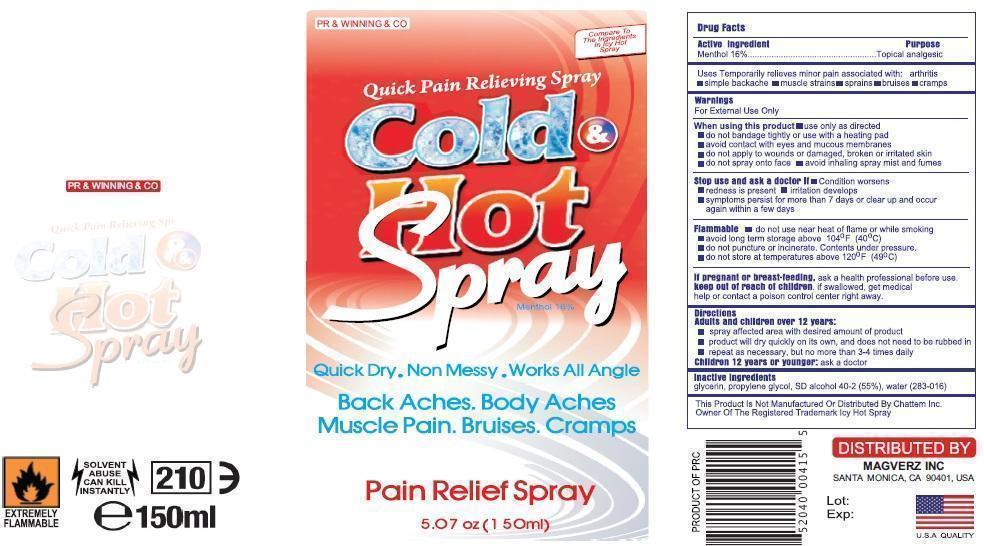 DRUG LABEL: Cold and Hot
NDC: 59240-002 | Form: SPRAY
Manufacturer: MAGVERZ INC
Category: otc | Type: HUMAN OTC DRUG LABEL
Date: 20130713

ACTIVE INGREDIENTS: MENTHOL 16 g/100 mL
INACTIVE INGREDIENTS: METHYL SALICYLATE; THYMOL; ZINC STEARATE

Cold and Hot Spray

Acitves

Menthol 16 %

Inactives

Glycerin.

Propylene Glycol

SD Alchohol 40-2(55%)

Water (283-016)

Uses

Temporarily relieves minor pain associated with:

arthritissimple

backachemuscle

strainss

prains

bruise

scramps

Indication

Temporarily relieves minor pain

Directions

Spray affected are with desired amount of product

Product will dry quickly on its own and doest not to be rubbed in

Repeat as necessary but not more than 3-4 times dilay

Warnings

For External use only

When using this product

Use only as directed

Do not bandage tightly or with heating pad

Avoid contact with eyes and mucous membranes

Do not apply to wounds or damagged, broken or irritated skin

Do not spray on face

Avoid inhaling spray mist and fumes

Stop use and ask docotor if;

Condition Worsesns

Redness is presnt for more than 7 days

Irritation developes

Symptomps persist for mor than 7 dyas or clear up and occur again within a few days.

Flamalble
Do not use near heat or flame or while smoking.

Avod long term storage above 104oF (40^0C)

Do not puncture of or incinerate.Congents under pressure.

Do not store at temreture above 120oF (49^0C)

If pregnant or breast feeding

Ask health professionals before use.

If sollowed get medical help or contact poison control center right away.

Keep Out of Reach of Childrens

Productt Label

Product Label